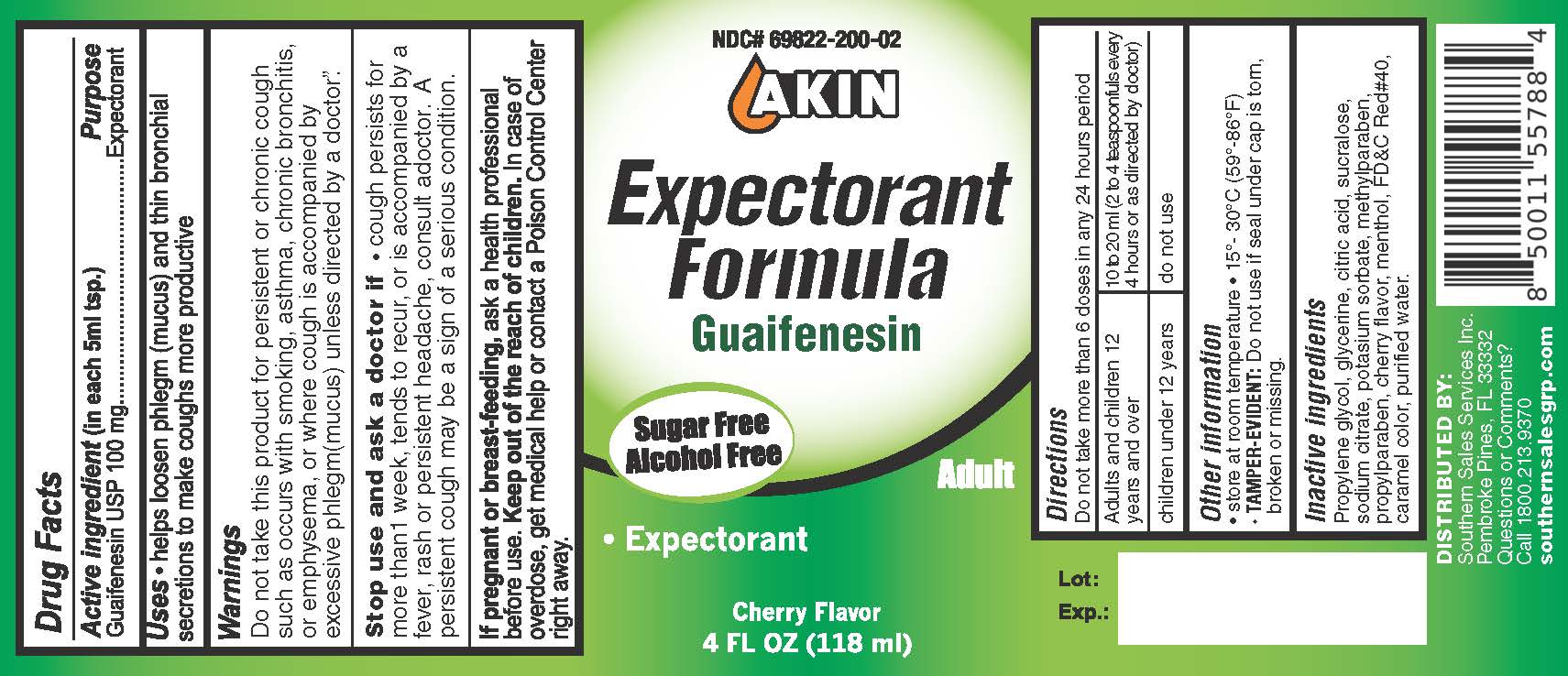 DRUG LABEL: Akin
NDC: 69822-200 | Form: SOLUTION
Manufacturer: Southern Sales & Service, Inc.
Category: otc | Type: HUMAN OTC DRUG LABEL
Date: 20231129

ACTIVE INGREDIENTS: GUAIFENESIN 100 mg/5 mL
INACTIVE INGREDIENTS: PROPYLENE GLYCOL; GLYCERIN; CITRIC ACID MONOHYDRATE; SUCRALOSE; SODIUM CITRATE; POTASSIUM SORBATE; MENTHOL; FD&C RED NO. 40; WATER

Akin Expectorant Formula

(in each 5ml tsp.) Active ingredient

Guaifenesin USP 100 mg

Purpose

Expectorant

Uses

helps loosen phlegm (mucus) and thin bronchial secretions to make coughs more productive

Warnings

Do not take this product for persistent or chronic couch such as occurs with smoking, asthma, chronic bronchitis, or emphysema, or where cough is accompanied by excessive phlegm(mucus) unless directed by a doctor."

Stop use

and ask a doctor if

cough persists for more than 1 week, tends to recur, or is accompanied by a fever, rash or persistent headache, consult a doctor. A persistent cough may be a sign of a serious condition.

If pregnant or breast-feeding,

ask a health professional before use.

Keep out of the reach of children.

In case of overdose, get medical help or contact a Poison Control Center right away.

Directions

Do not take more than 6 doses in any 24-hour period.

adults and children 12 years and over | 10 to 20 ml (2 to 4 teaspoonfuls every 4 hours or as directed by doctor)
children under 12 years | do not use

Other information

- store at room temperature
- 15°-30°C (59°-86°F)
- Do not use if seal under cap is torn, broken or missing. TAMPER-EVIDENT:

Inactive ingredients

Propylene glycol, glycerine, citric acid, sucralose, sodium citrate, potasium sorbate, methylparaben, propylparaben, cherry flavor, menthol, FD &C Red # 40, caramel color, purified water.